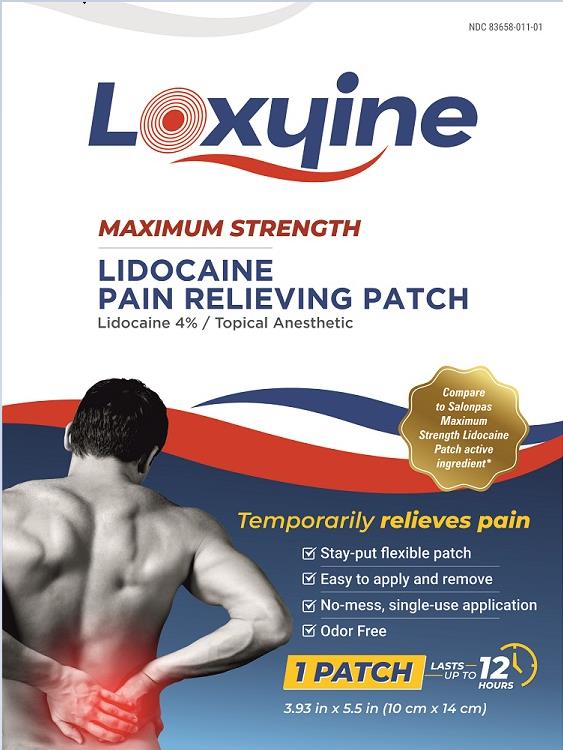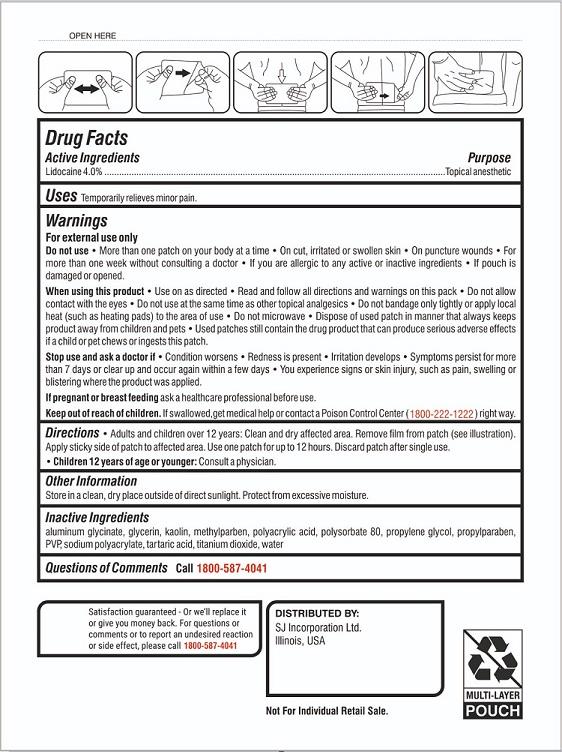 DRUG LABEL: Loxyine
NDC: 83658-011 | Form: PATCH
Manufacturer: Sj Incorporation Ltd
Category: otc | Type: HUMAN OTC DRUG LABEL
Date: 20231120

ACTIVE INGREDIENTS: LIDOCAINE 4 mg/100 mg
INACTIVE INGREDIENTS: ALUMINIUM TRIGLYCINATE; GLYCERIN; KAOLIN; METHYLPARABEN; POLYACRYLIC ACID (8000 MW); POLYSORBATE 80; PROPYLENE GLYCOL; PROPYLPARABEN; SODIUM POLYACRYLATE (8000 MW); TARTARIC ACID; TITANIUM DIOXIDE; WATER

Loxyine
Maximum Strength
Lidocaine
Pain Relieving Patch

Active ingredient

Lidocaine 4.0%

Purpose

Topical anesthetic

Uses

Temporarily relieves minor pain.

Warnings

For external use only

Do not use

- more than one patch on your body at a time
- On cut, irritated or swollen skin
- On puncture wounds
- For more than one week without consulting a doctor
- If you are allergic to any active or inactive ingredients
- If pouch is damaged or opened.

When using this product

- use only as directed
- Read and follow all directions and warning on this pack
- Do not allow contact with the eyes
- Do not use at the same time as other topical analgesics
- Do not bandage only tightly or apply local heat (such as heating pads) to the area of use
- Do not microwave
- Dispose of used patch in manner that always keeps product away from children and pets
- Used patches still contain the drug product that can produce serious adverse effects if a child or pet chews or ingests this patch.

Stop use and ask a doctor if

- Condition worsens
- Redness is present
- Irritation develops
- Symptoms persist for more than 7 days or clear up and occur again within a few days
- You experience signs or skin injury, such as pain, swelling or blistering where the product was applied.

If pregnant or breast-feeding,

ask a healthcare professional before use.

Keep out of reach of children.

If swallowed, get medical help or contact a Poison Control Center (1800-222-1222) right away.

Directions

Adults and children 12 years of age and over: Clean and dry affected area. Remove film from patch (see illustration). Apply sticky side of patch to affected area. Use one path for up to 12 hours. Discard patch after single use.

Children under 12 years of age: Consult a physician.

Other information

Store in a clean, dry place outside of direct sunlight. Protect from excessive moisture.

Inactive ingredients

aluminum glycinate, glycerin, kaolin, methylparaben, polyacrylic acid, polysorbate 80, propylene glycol, propylparaben, PVP, sodium polyacrylate, tartaric acid, titanium dioxide, water.

Questions or comments?

Toll free 1-800-587-4041